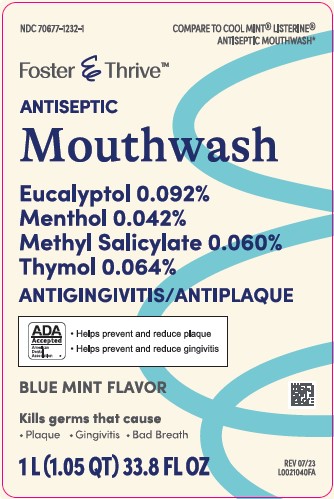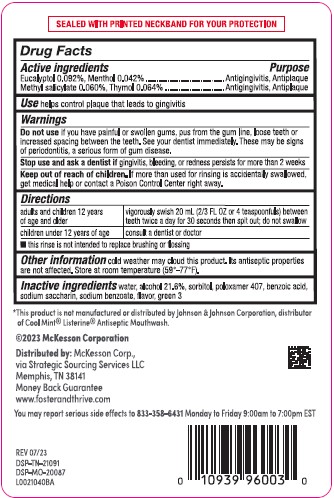 DRUG LABEL: Eucalyptol, Menthol, Methyl Salicylate, Thymol
NDC: 70677-1232 | Form: MOUTHWASH
Manufacturer: Strategic Sourcing Services LLC
Category: otc | Type: HUMAN OTC DRUG LABEL
Date: 20260217

ACTIVE INGREDIENTS: EUCALYPTOL 0.92 mg/1 mL; MENTHOL 0.42 mg/1 mL; METHYL SALICYLATE 0.6 mg/1 mL; THYMOL 0.64 mg/1 mL
INACTIVE INGREDIENTS: WATER; ALCOHOL; SORBITOL; POLOXAMER 407; BENZOIC ACID; SACCHARIN SODIUM; SODIUM BENZOATE; FD&C GREEN NO. 3

Foster & Thrive 664.003/664AT rev2-664AU
Blue Mint Antiseptic Mouthrinse

Tamper Evident Statement

SEALED WITH PRINTED NECKBAND FOR YOUR PROTECTION

Active ingredients

Eucalyptol 0.092%

Menthol 0.042%

Methyl salicylate 0.060%

Thymol 0.064%

Purpose

Antigingivitis, Antiplaque

Use

helps control plaque that leads to gingivitis

Warnings

for this product

Do not use

if you have painful or swollen gums, pus from the gum line, loose teeth or increased spacing between the teeth. See your dentist immediately. These may be signs of periodontitis, a serious form of gum disease.

Stop use and ask a dentist if

gingivitis, bleeding, or redness persists for more than 2 weeks.

Keep out of reach of children.

If more than used for rinsing is accidentally swallowed, get medical help or contact a Poison Control Center right away.

Directions

adults and children 12 years of age and older - vigorously swish 20 mL (2/3 FL OZ or 4 teaspoonfuls) between teeth twice a day for 30 seconds then spit out.

children under 12 years of age - consult a dentist or doctor

- this rinse is not intended to replace brushing or flossing

Other information

cold weather may cloud this product. Its antiseptic properties are not affected. Store at room temperature (59°-77°F)

Inactive ingredients

water, alcohol 21.6%, sorbitol, poloxamer 407, benzoic acid, sodium saccharin, sodium benzoate, flavor, green 3

Disclaimer

*This product is not manufactured or distributed by Johnson & Johnson Corporation, distributer of Cool Mint®Listerine®Antiseptic Mouthwash.

Adverse Reactions

©2023 McKesson Corporation

Distributed by: Mckesson Corp.,

via Strategic Sourcing Services LLC

Memphis, TN 38141

Money Back Guarantee

www.foster&thrive.com

You may report serious side effects to 833-358-6431 Monday to Friday 9:00am to 7:00pm EST

REV 07/23

DSP-TN-21091

DSP-MO-20087

Principal display panel

NDC 70677-1232-1

COMPARE TO COOL MINT®LISTERINE®ANTISEPTIC MOUTHWASH*

Foster & Thrive™

ANTISEPTIC

Mouthwash

Eucalyptol 0.092%

Menthol 0.042%

Methyl Salicylate 0.060%

Thymol 0.064%

ANTIGINGIVITIS/ANTIPLAQUE

ADA Accepted

American Dential Association

- Helps prevent and reduce plaque
- Helps prevent and reduce gingivitis

BLUE MINT FLAVOR

Kills germs that cause

- Plaque
- Gingivitis
- Bad Breath

1 L (1.05 QT) 33.8 FL OZ